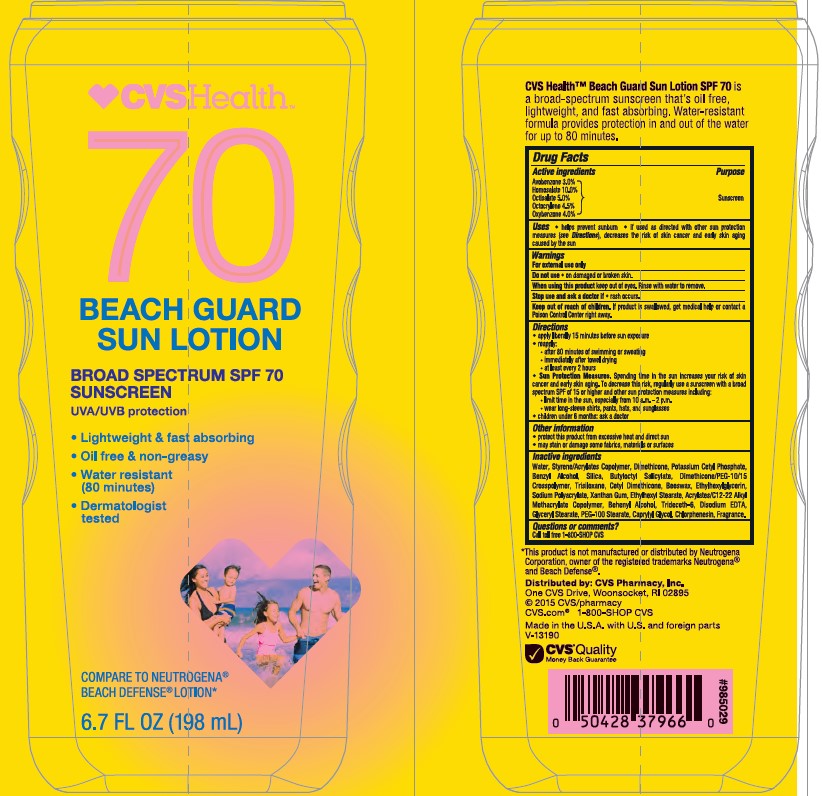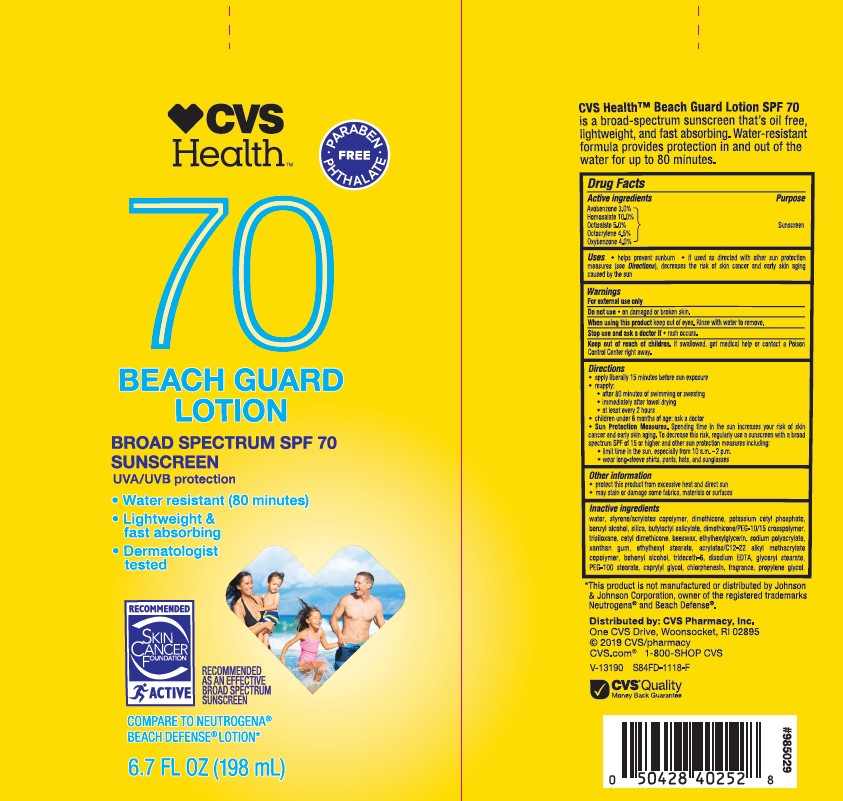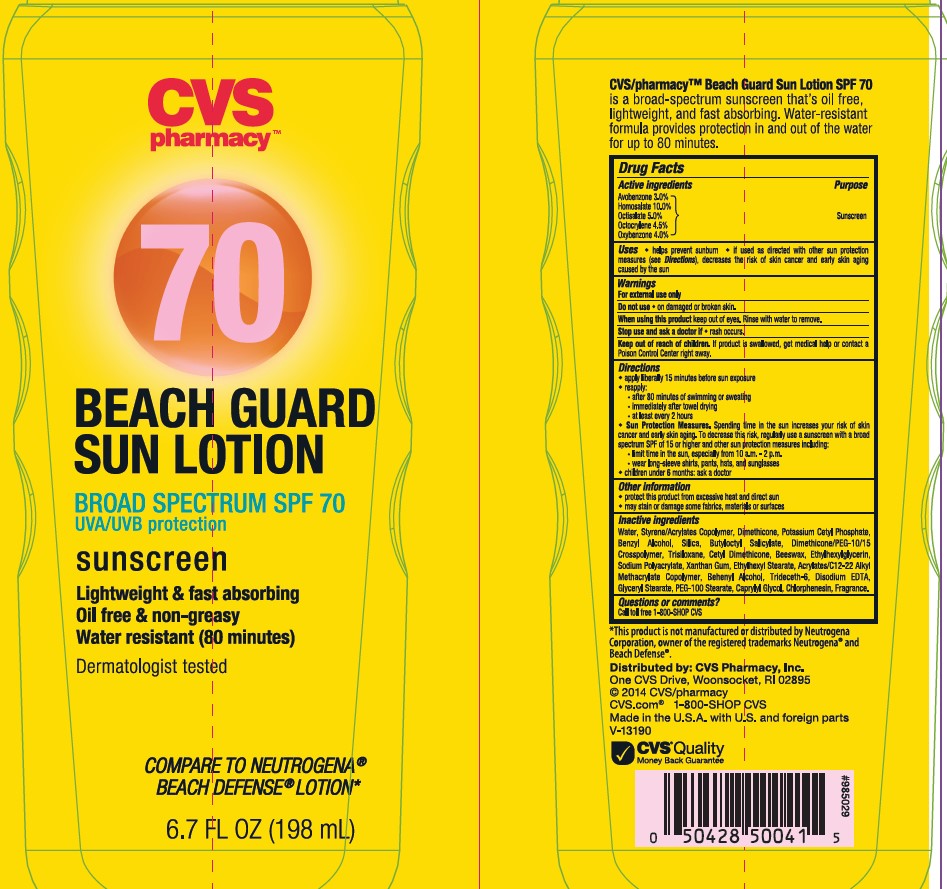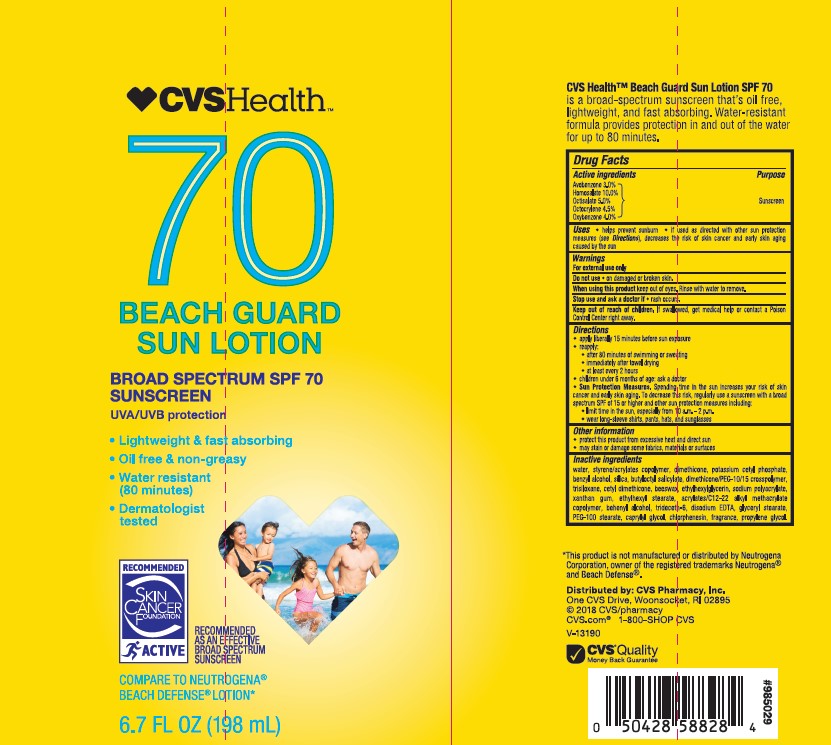 DRUG LABEL: CVS Health
NDC: 69842-148 | Form: LOTION
Manufacturer: CVS Pharmacy
Category: otc | Type: HUMAN OTC DRUG LABEL
Date: 20241022

ACTIVE INGREDIENTS: OCTOCRYLENE 45 mg/1 mL; OCTISALATE 50 mg/1 mL; HOMOSALATE 100 mg/1 mL; AVOBENZONE 30 mg/1 mL; OXYBENZONE 40 mg/1 mL
INACTIVE INGREDIENTS: DIMETHICONE; POTASSIUM CETYL PHOSPHATE; BENZYL ALCOHOL; BUTYLOCTYL SALICYLATE; BUTYL ACRYLATE/C16-C20 ALKYL METHACRYLATE/METHACRYLIC ACID/METHYL METHACRYLATE COPOLYMER; CAPRYLYL GLYCOL; SILICON DIOXIDE; WATER; ETHYLHEXYLGLYCERIN; PROPYLENE GLYCOL; TRISILOXANE; DOCOSANOL; SODIUM POLYACRYLATE (8000 MW); CETYL DIMETHICONE 150; WHITE WAX; ETHYLHEXYL STEARATE; TRIDECETH-6; GLYCERYL STEARATE/PEG-100 STEARATE; XANTHAN GUM; BUTYL METHACRYLATE/METHYL METHACRYLATE/METHACRYLIC ACID/STYRENE CROSSPOLYMER; EDETATE DISODIUM; CHLORPHENESIN

CVS Health SPF 70 Beach Guard Sun Lotion

Active ingredients

Avobenzone 3.0%, Homosalate 10.0%, Octisalate 5.0%, Octocrylene 4.5%, Oxybenzone 4.0%

Purpose

Sunscreen

Uses

- helps prevent sunburn
- if used as directed with other sun protection measures (see Directions), decreases the risk of skin cancer and early skin aging caused by the sun

Warnings

For external use only

Do not use

- on damaged or broken skin

When using this product

keep out of eyes. Rinse with water to remove.

Stop use and ask a doctor if

- rash occurs.

Keep out of reach of children.

If product is swallowed, get medical help or contact a Poison Control Center right away.

Directions

• apply liberally 15 minutes before sun exposure
reapply:
• after 80 minutes of swimming or sweating
• immediately after towel drying
• at least every 2 hours

• children under 6 months: Ask a doctor

Sun Protection Measures. Spending time in the sun increases your risk of skin cancer and early skin aging. To decrease this risk, regularly use a sunscreen with a Broad Spectrum SPF value of 15 or higher and other sun protection measures including:
• limit time in the sun, especially from 10 a.m. - 2 p.m.
• wear long-sleeved shirts, pants, hats, and sunglasses

Other information

• protect the product in this container from excessive heat and direct sun
• may stain or damage some fabrics, materials or surfaces

Inactive ingredients

Water, Styrene/Acrylates Copolymer, Dimethicone, Potassium Cetyl Phosphate, Benzyl Alcohol, Silica, Butyloctyl Salicylate, Dimethicone/PEG-10/15 Crosspolymer, Trisiloxane, Cetyl Dimethicone, Beeswax, Ethylhexylglycerin, Sodium Polyacrylate, Xanthan Gum, Ethylhexyl Stearate, Acrylates/C12-22 Alkyl Methacrylate Copolymer, Behenyl Alcohol, Trideceth-6, Disodium EDTA, Glyceryl Stearate, PEG-100 Stearate, Caprylyl Glycol, Chlorphenesin, Fragrance, Propylene Glycol.

Labels

CVS HEALTH SPF 70 BEACH GUARD SUN LOTION BROAD SPECTRUM SPF 70 SUNSCREEN

6.7 FL OZ (198 mL)

NDC 69842-148-27